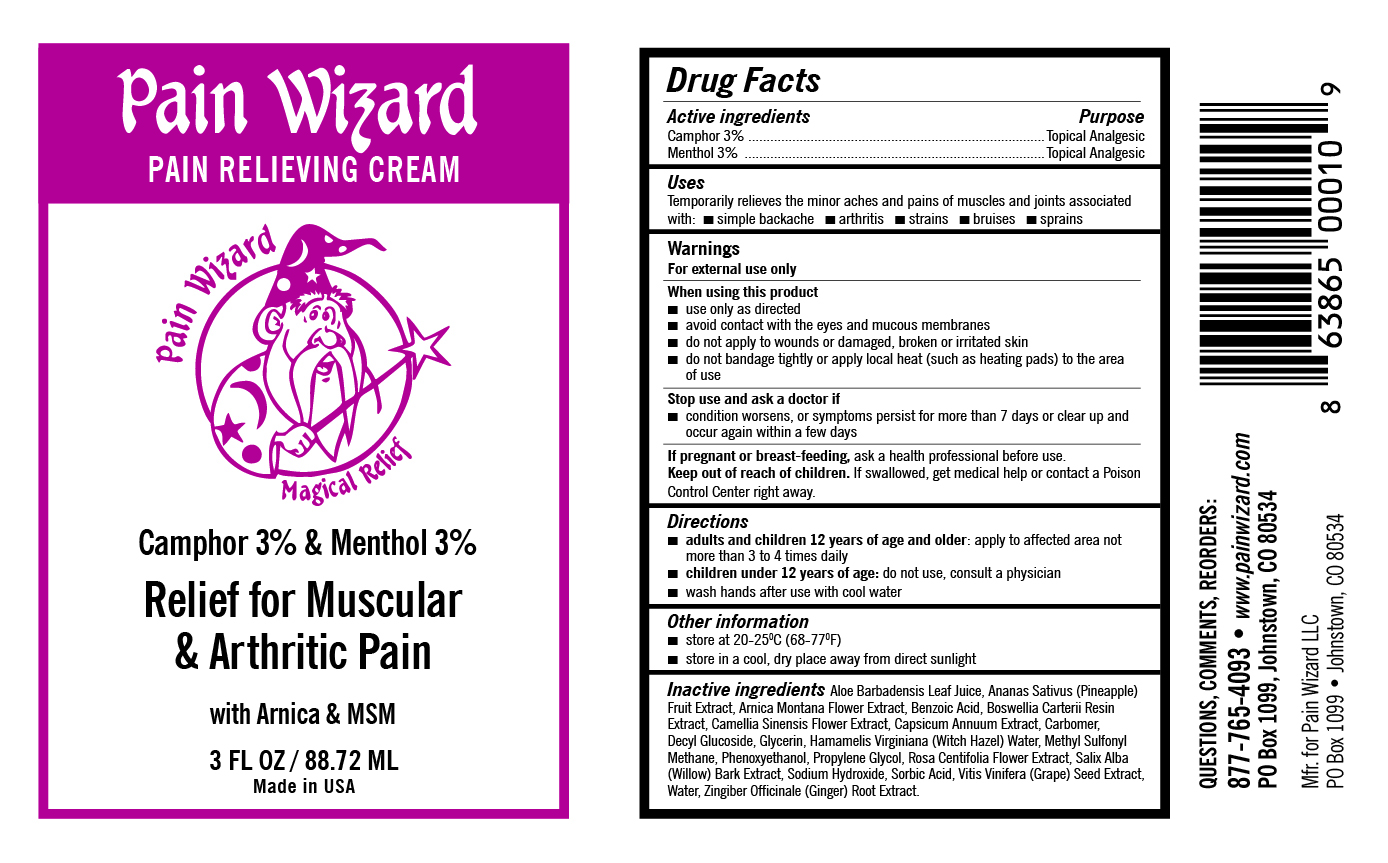 DRUG LABEL: Pain Relieving Cream
NDC: 84338-001 | Form: CREAM
Manufacturer: PAIN WIZARD LIMITED LIABILITY COMPANY
Category: otc | Type: HUMAN OTC DRUG LABEL
Date: 20260105

ACTIVE INGREDIENTS: CAMPHOR (SYNTHETIC) 3 mg/100 mL; MENTHOL 3 mg/100 mL
INACTIVE INGREDIENTS: BENZOIC ACID; VITIS VINIFERA SEED; SALIX ALBA BARK; ALOE VERA LEAF; ROSA CENTIFOLIA FLOWER; ARNICA MONTANA FLOWER; CAPSICUM; DECYL GLUCOSIDE; DIMETHYL SULFONE; SORBIC ACID; GINGER; SODIUM HYDROXIDE; PROPYLENE GLYCOL; FRANKINCENSE; PHENOXYETHANOL; WATER; CAMELLIA SINENSIS FLOWER; ANANAS SATIVUS (PINEAPPLE) FRUIT; HAMAMELIS VIRGINIANA TOP WATER; GLYCERIN; CARBOMER COPOLYMER TYPE C (ALLYL PENTAERYTHRITOL CROSSLINKED)

Active ingredients

Camphor 3%

Menthol 3%

Purpose

Topical Analgesic

Uses

Temporarily relieves the minor aches and pains of muscles and joints associated with:

- simple backache
- arthritis
- sprains
- bruises
- strains

Warnings

For external use only

When using this product

- use only as directed
- avoid contact with the eyes and mucous membranes
- do not apply to wounds or damaged, broken or irritated skin
- do not bandage tightly or apply local heat (such as heating pads) to the area of use

Stop use and ask a doctor if

- condition worsens, or symptoms persist for more than 7 days or clear up and occur again within a few days

PREGNANCY OR BREAST FEEDING

If pregnant or breast-feeding, ask a health professional before use.

Keep out of reach of children. If swallowed, get medical help or contact a Poison Control Center right away.

Directions

- adults and children 12 years of age and older: apply to affected area not more than 3 to 4 times daily
- children under 12 years of age: do not use, consult a physician
- wash hands after use with cool water

Other information

- store at 20-25°C (68-77°F)
- store in a cool, dry place away from direct sunlight

Inactive ingredients

Aloe Barbadensis Leaf Juice, Ananas Sativus (Pineapple) Fruit Extract, Arnica Montana Flower Extract, Benzoic Acid, Boswellia Carterii Resin Extract, Camellia Sinensis Flower Extract, Capsicum Annuum Extract, Carbomer, Decyl Glucoside, Glycerin, Hamamelis Virginiana (Witch Hazel) Water, Methyl Sulfonyl Methane, Phenoxyethanol, Propylene Glycol, Rosa Centifolia Flower Extract, Salix Alba (Willow) Bark Extract, Sodium Hydroxide, Sorbic Acid, Vitis Vinifera (Grape) Seed Extract, Water, Zingiber Officinale (Ginger) Root Extract

PACKAGE LABEL

Pain Wizard

PAIN RELIEVING CREAM

Camphor 3% & Menthol 3%

Relief for Muscular & Arthritic Pain

with Arnica & MSM

3 FL OZ / 88.72 ML

Made in USA